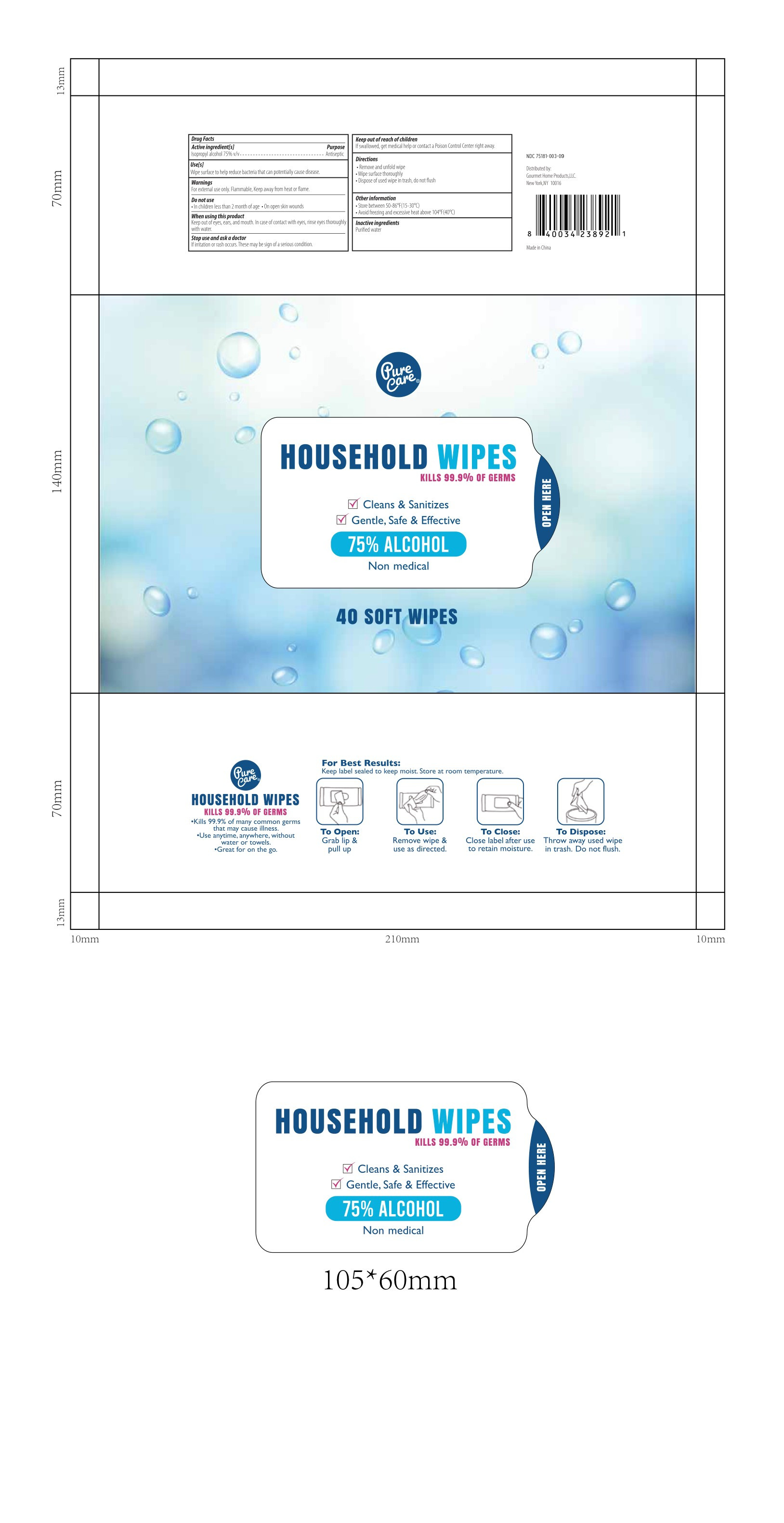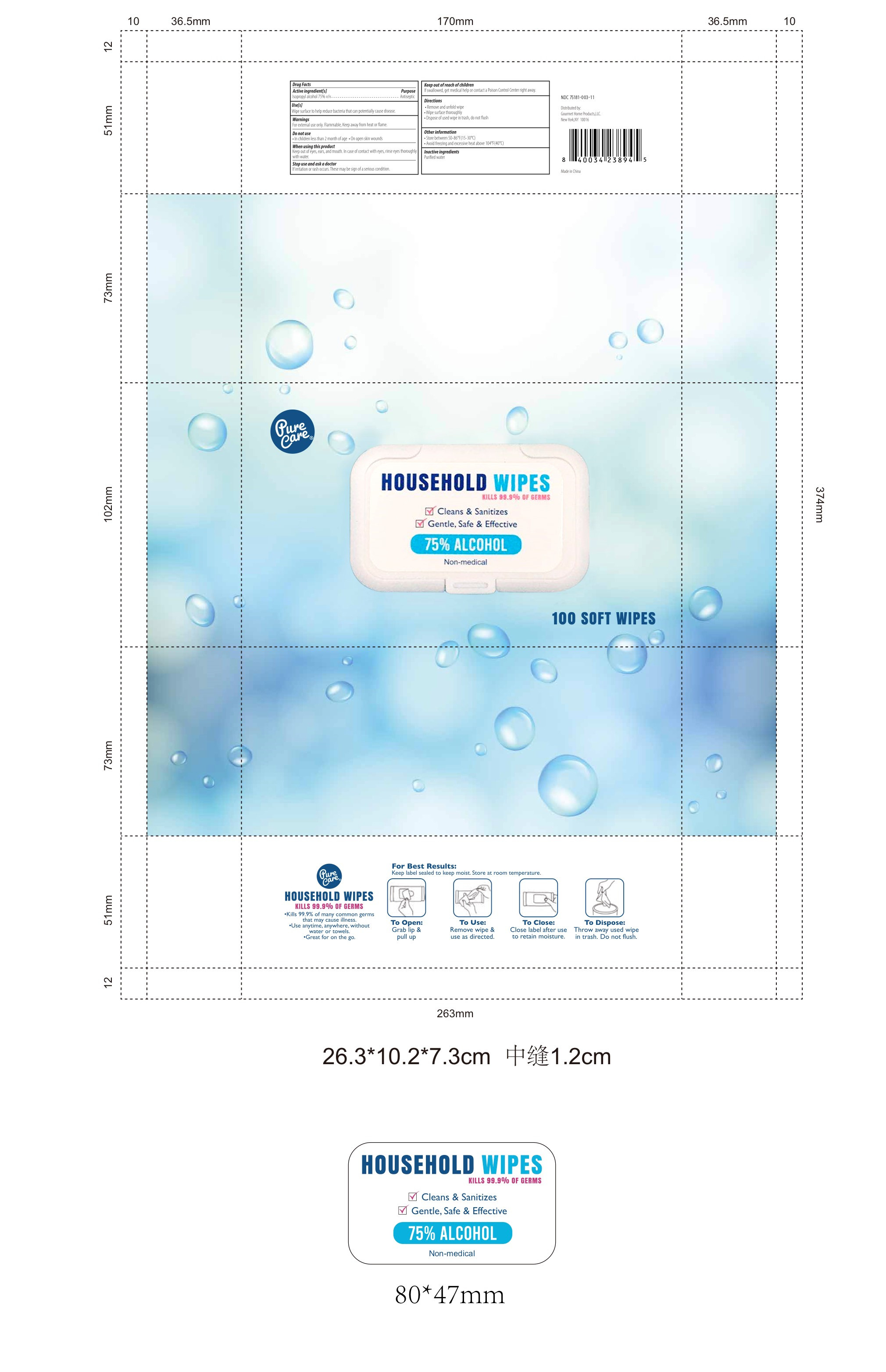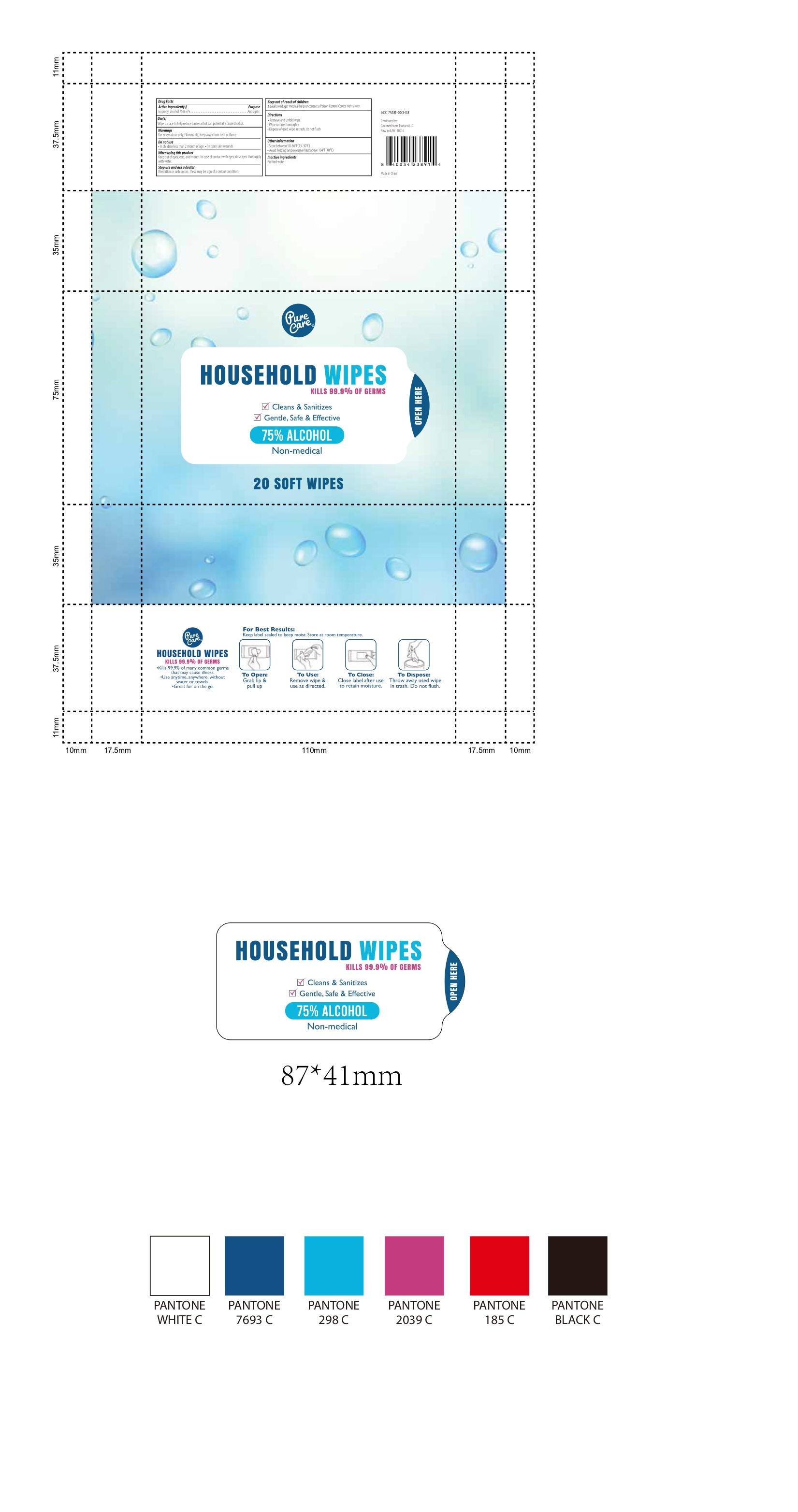 DRUG LABEL: Household wipes
NDC: 55487-001 | Form: CLOTH
Manufacturer: Ningbo MKL Commodity Co., Ltd.
Category: otc | Type: HUMAN OTC DRUG LABEL
Date: 20200723

ACTIVE INGREDIENTS: ALCOHOL 120 mL/40 1
INACTIVE INGREDIENTS: ALOE VERA LEAF; WATER; GLYCERIN

DOSAGE AND ADMINISTRATION

1. Store between 50-86°F(15-30°)
2.Avoid feezing and exessive heat above 104°F(40°C)

INACTIVE INGREDIENT

Aqua,Glycerin,aloe barbadensis leaf juice

INDICATIONS AND USAGE

1.Remove and unfold wipe
2.Wipe surface thoroughly
3.Dispose of used wipe intrash, do not flush

ACTIVE INGREDIENT

Ethanol

keep out of reach of children

PURPOSE

Disinfection
Sterilization
No Rinseing

WARNINGS

For external use only. Fammable, Keep away from heat or flame.